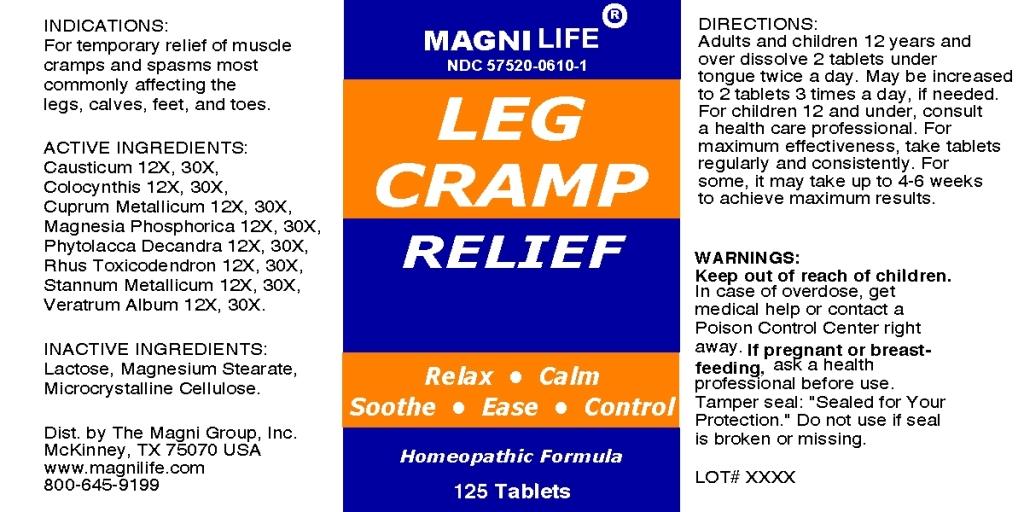 DRUG LABEL: Leg Cramp Relief
NDC: 57520-0610 | Form: TABLET
Manufacturer: Apotheca Company
Category: homeopathic | Type: HUMAN OTC DRUG LABEL
Date: 20110223

ACTIVE INGREDIENTS: MAGNESIUM PHOSPHATE, DIBASIC TRIHYDRATE 30 [hp_X]/1 1; COPPER 30 [hp_X]/1 1; CITRULLUS COLOCYNTHIS FRUIT PULP 30 [hp_X]/1 1; PHYTOLACCA AMERICANA ROOT 30 [hp_X]/1 1; VERATRUM ALBUM ROOT 30 [hp_X]/1 1; TIN 30 [hp_X]/1 1; TOXICODENDRON PUBESCENS LEAF 30 [hp_X]/1 1; CAUSTICUM 30 [hp_X]/1 1
INACTIVE INGREDIENTS: CELLULOSE, MICROCRYSTALLINE; LACTOSE; MAGNESIUM STEARATE

Leg Cramp Relief

ACTIVE INGREDIENT

ACTIVE INGREDIENTS: Magnesia phosphorica 12X, 30X, Cuprum metallicum 12X, 30X, Colocynthis 12X, 30X, Phytolacca decandra 12X, 30X, Veratrum alum 12X, 30X, Causticum 12X, 30X, Stannum metallicum 12X, 30X, Rhus toxicodendron 12X, 30X.

PURPOSE

INDICATIONS: For temporary relief of muscle cramps and spasms most commonly affecting the legs, calves, feet and toes.

WARNINGS

WARNINGS: Keep out of reach of children. In case of overdose, get medical help or contact a Poison Control Center right away.

If pregnant or breast-feeding, ask a health professional before use.

Tamper seal: "Sealed for Your Protection." Do not use if seal is broken or missing.

DOSAGE AND ADMINISTRATION

DIRECTIONS: Adults and children 12 years and over dissolve 2 tablets under tongue twice a day. May be increased to 2 tablets 3 times a day, if needed. For children 12 and under, consult a health care professional. For maximum effectiveness, take tablets regularly and consistently. For some, it may take up to 4-6 weeks to achieve maximum results.

INACTIVE INGREDIENT

INACTIVE INGREDIENTS: Lactose, Magnesium stearate, Microcrystalline cellulose.

KEEP OUT OF REACH OF CHILDREN. In case of overdose, get medical help or contact a Poison Control Center right away.

INDICATIONS AND USAGE

INDICATIONS: For temporary relief of muscle cramps and spasms most commonly affecting the legs, calves, feet, and toes.

QUESTIONS

Dist. by The Magni Group, Inc.

McKinney, TX 75075 USA

www.magnilife.com

800-645-9199

PACKAGE LABEL

MAGNILIFE

NDC 57520-0610-1

LEG CRAMP RELIEF

Relax Calm Soothe Ease Control

Homeopathic Formula

125 Tablets